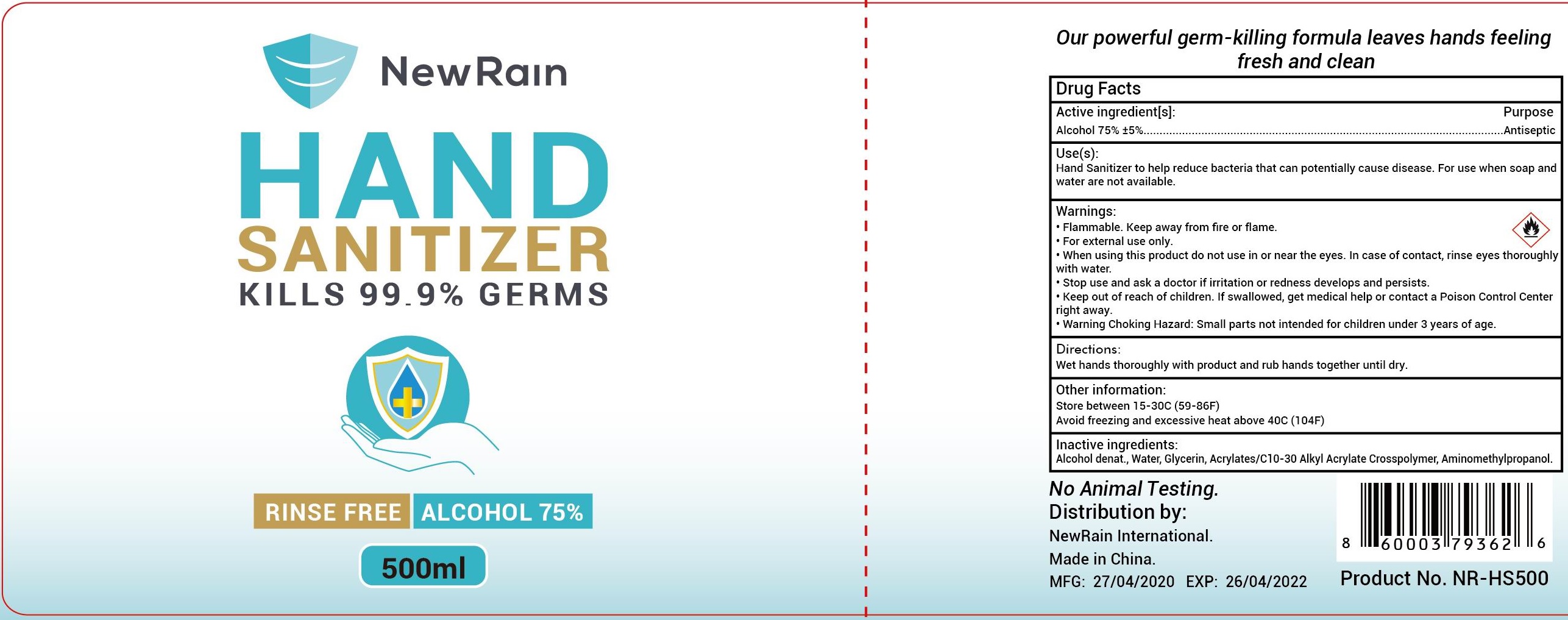 DRUG LABEL: NewRain Hand Sanitizer
NDC: 56136-312 | Form: GEL
Manufacturer: Ganzhou Olivee Cosmetic Co., Ltd.
Category: otc | Type: HUMAN OTC DRUG LABEL
Date: 20200430

ACTIVE INGREDIENTS: ALCOHOL 75 mL/100 mL
INACTIVE INGREDIENTS: WATER; CARBOMER INTERPOLYMER TYPE A (ALLYL SUCROSE CROSSLINKED); AMINOMETHYLPROPANOL; CARBOMER COPOLYMER TYPE A; .ALPHA.-TOCOPHEROL ACETATE, DL-; GLYCERIN

OPALINE HAND SANITIZER

Active ingredient

Alcohol 75% ±5%

Purpose

Antiseptic

Use(s)

Hand Sanitizer to help reduce bacteria that can potentially cause disease. For use when soap and water are not available.

Warnings

For external use only.

Flammable. Keep product away from fire or flame.

When using this prouct do not use in or near the eye. In case of contact, rine eyes thoroughly with water.

Stop use and ask a doctor if

irritation or redness develops and persists.

Other Information:

store between 15-30℃ (59-86℉)

avoid freezing and excssive heat above 40℃（104℉）.

Keep out of reach of children.

If swallowed, get medical help or contact a Poison Control Center right away.

Warning choking Hazard: Small Parts. Not intended for children under 3 years of age.

Directions

Wet hands thoroughly with product and rub hands together until dry.

Inactive ingredients

Alcohol Denat, Water (Aqua), Glycerin, Acrylates/C10-30 Alkyl Acrylate Crosspolymer, Aminomethyl Propanol